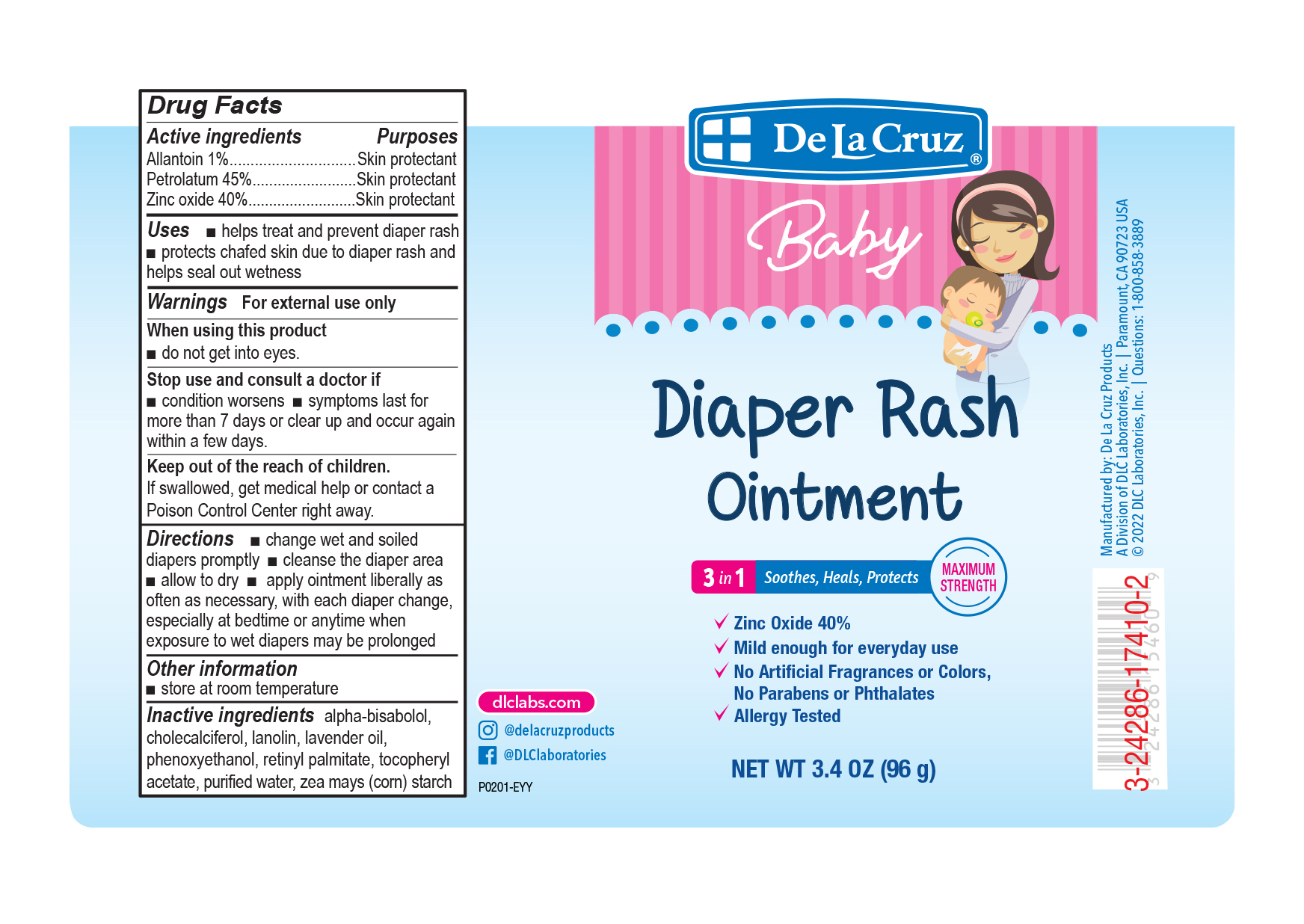 DRUG LABEL: DE LA CRUZ DIAPER RASH
NDC: 24286-1566 | Form: OINTMENT
Manufacturer: DLC Laboratories, Inc.
Category: otc | Type: HUMAN OTC DRUG LABEL
Date: 20260107

ACTIVE INGREDIENTS: ALLANTOIN 1 g/100 g; PETROLATUM 45 g/100 g; ZINC OXIDE 40 g/100 g
INACTIVE INGREDIENTS: LANOLIN; WATER; PHENOXYETHANOL; .ALPHA.-TOCOPHEROL ACETATE; STARCH, CORN; LAVENDER OIL; VITAMIN A PALMITATE; CHOLECALCIFEROL; LEVOMENOL

DE LA CRUZ®DIAPER RASH OINTMENT

Drug Facts

ACTIVE INGREDIENT

Active ingredients | Purpose
Allantoin 1% | Skin protectant
Petrolatum 45% | Skin protectant
Zinc oxide 40% | Skin protectant

Uses

- helps treat and prevent diaper rash
- protects chafed skin due to diaper rash and helps seal out wetness

Warnings

For external use only.

When using this product

- do not get into eyes

Stop use and ask a doctor if

- condition worsens
- symptoms last for more than 7 days or clear up and occur again within a few days

KEEP OUT OF REACH OF CHILDREN

Keep out of the reach of children.If swallowed, get medical help or contact a Poison Control Center right away.

Directions

- change wet and soiled diapers promptly
- cleanse the diaper area
- allow to dry
- apply ointment liberally as often as necessary, with each diaper change, especially at bedtime or anytime when exposure to wet diapers may be prolonged

Other information

- store at room temperature

Inactive ingredients

alpha-bisabolol, cholecalciferol, lanolin, lavender oil, phenoxyethanol, retinyl palmitate, tocopheryl acetate, purified water, zea mays (corn) starch

Questions

1-800-858-3889

Manufactured by:
De La Cruz Products
A Division of DLC Laboratories, Inc.
Paramount, CA 90723 USA

PRINCIPAL DISPLAY PANEL - 96 g Tube Label

De La Cruz®

Baby

Diaper Rash
Ointment

3 in 1
Soothes, Heals, Protects
MAXIMUM
STRENGTH

- Zinc Oxide 40%
- Mild enough for everyday use
- No Artificial Fragrances or Colors,
  No Parabens or Phthalates
- Allergy Tested

NET WT 3.4 OZ (96 g)